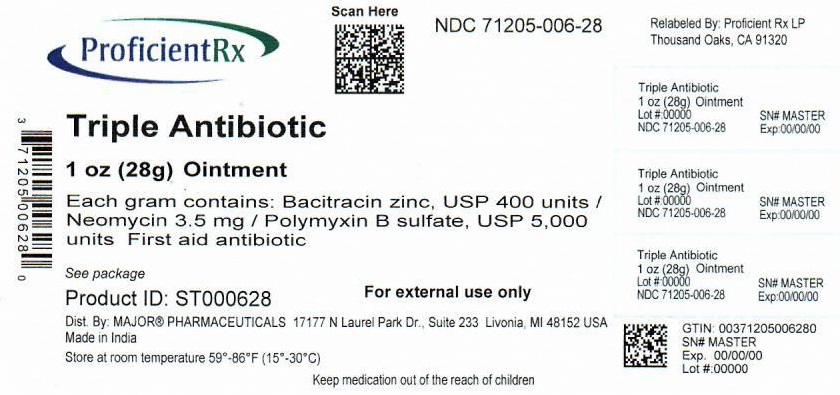 DRUG LABEL: TRIPLE ANTIBIOTIC
NDC: 71205-006 | Form: OINTMENT
Manufacturer: Proficient Rx LP
Category: otc | Type: HUMAN OTC DRUG LABEL
Date: 20240101

ACTIVE INGREDIENTS: BACITRACIN ZINC 400 [iU]/1 g; NEOMYCIN SULFATE 3.5 mg/1 g; POLYMYXIN B SULFATE 5000 [iU]/1 g
INACTIVE INGREDIENTS: PETROLATUM

Triple Antibiotic Ointment (Bacitracin Zinc, Neomycin Sulfate, Polymyxin B Sulfate)

Active ingredients (in each gram)

Bacitracin zinc, USP 400 units
Neomycin 3.5 mg
Polymyxin B sulfate, USP 5,000 units

Purpose

First aid antibiotic

Uses

First aid to help prevent infection in

- minor cuts
- scrapes
- burns

Warnings

For external use only

Allergy alert:

- do not use if allergic to any of the ingredients

Do not use

- in the eyes
- over large areas of the body

Ask a doctor before use if you have

- deep or puncture wounds
- animal bites
- serious burns

When using this product

- do not use longer than 1 week unless directed by a doctor

Stop use and ask a doctor if

- condition persists or gets worse
- a rash or other allergic reaction develops

Keep out of reach of children.

If swallowed, get medical help or contact a Poison Control Center right away.

Directions

- clean affected area
- apply a small amount of this product (an amount equal to the surface area of the tip of a finger) on the area 1 to 3 times daily
- may be covered with a sterile bandage

Other information

- Store at controlled room temperature 59°-86°F (15°-30°C). Protect from freezing.
- Before using any medication, read all label directions. Keep carton, it contains important information.

Inactive ingredient

white petrolatum

Questions?

1-800-432-8534 between 9 am and 4 pm EST, Monday–Friday.

Principal Display Panel

Distributed by:

MAJOR® PHARMACEUTICALS

Livonia, MI 48152

Product of India

Relabeled by:

Proficient Rx LP

Thousand Oaks, CA 91320

Protection Against Infection

NDC 71205-006-28

ORIGINAL STRENGTH
TRIPLE ANTIBIOTIC OINTMENT
Bacitracin Zinc–Neomycin Sulfate–Polymyxin B Sulfate
FIRST AID ANTIBIOTIC

Compare to the Active Ingredients in Neosporin®*
NET WT 1 oz (28g)